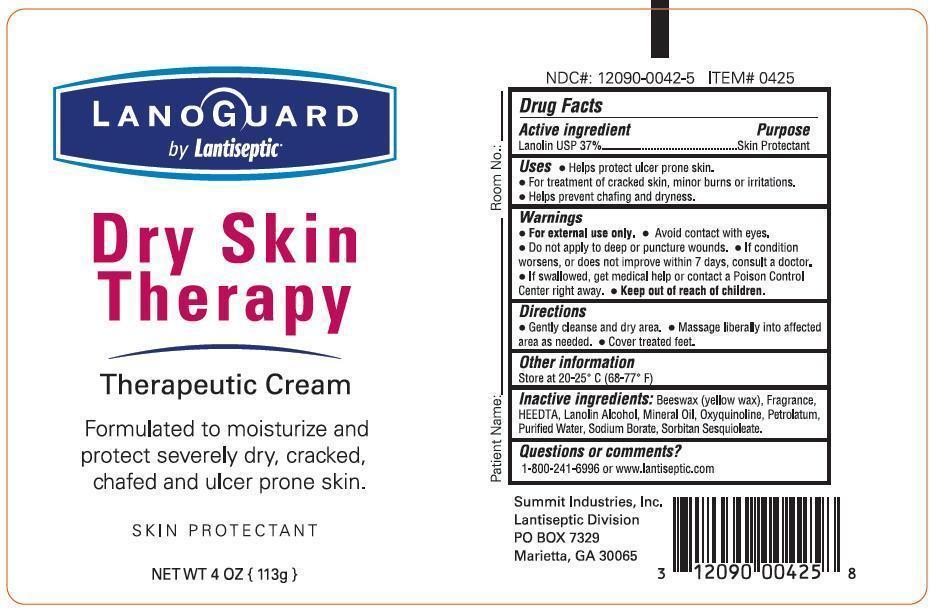 DRUG LABEL: LanoGuard
NDC: 12090-0042 | Form: CREAM
Manufacturer: Summit Industries, Inc.
Category: otc | Type: HUMAN OTC DRUG LABEL
Date: 20130321

ACTIVE INGREDIENTS: LANOLIN 370 mg/1 g
INACTIVE INGREDIENTS: YELLOW WAX; HYDROXYETHYLETHYLENEDIAMINETRIACETIC ACID; LANOLIN ALCOHOLS; MINERAL OIL; OXYQUINOLINE; PETROLATUM; WATER; SODIUM BORATE; SORBITAN SESQUIOLEATE

LanoGuard Dry Skin Therapy Therapeutic Cream Drug Facts

Active Ingredient

Lanolin USP 37%

Purpose

Skin Protectant

Uses

- Helps protect ulcer prone skin.
- For treatment of cracked skin, minor burns or irritation.
- Helps prevent chafing and dryness.

Warnings

- For external use only.
- Avoid contact with eyes.
- Do not apply to deep or puncture wounds.
- If condition worsens, or does not improve within 7 days, consult a doctor.
- If swallowed, get medical help or contact a Poison Control Center right away.

- Keep out of reach of children.

Directions

- Gently cleanse and dry area.
- Massage liberally into affected area as needed.
- Cover treated feet.

Other Information

Store at 20-25°C (68-77°F)

Inactive Ingredients:

Beeswax (yellow wax), Fragrance, HEEDTA, Lanolin Alcohol, Mineral Oil, Oxyquinoline, Petrolatum, Purified Water, Sodium Borate, Sorbitan Sesquioleate

Questions Comments?

1-800-241-6996 or www.lantiseptic.com

SUMMIT INDUSTRIES, INC

Lantiseptic Division

PO BOX 7329

Marietta, GA 30065

Image of representative artwork

LanoGuardDrySkinfouroz.jpg